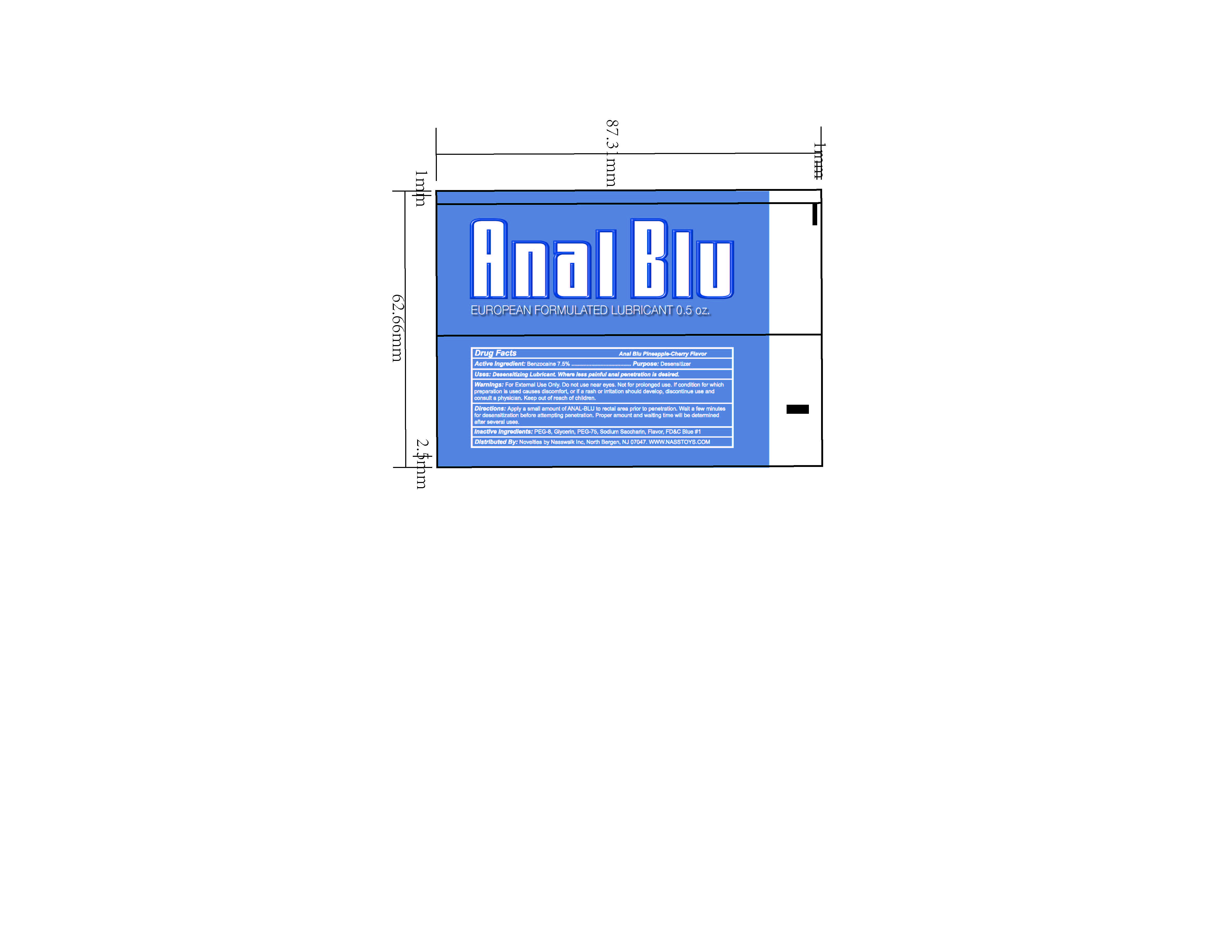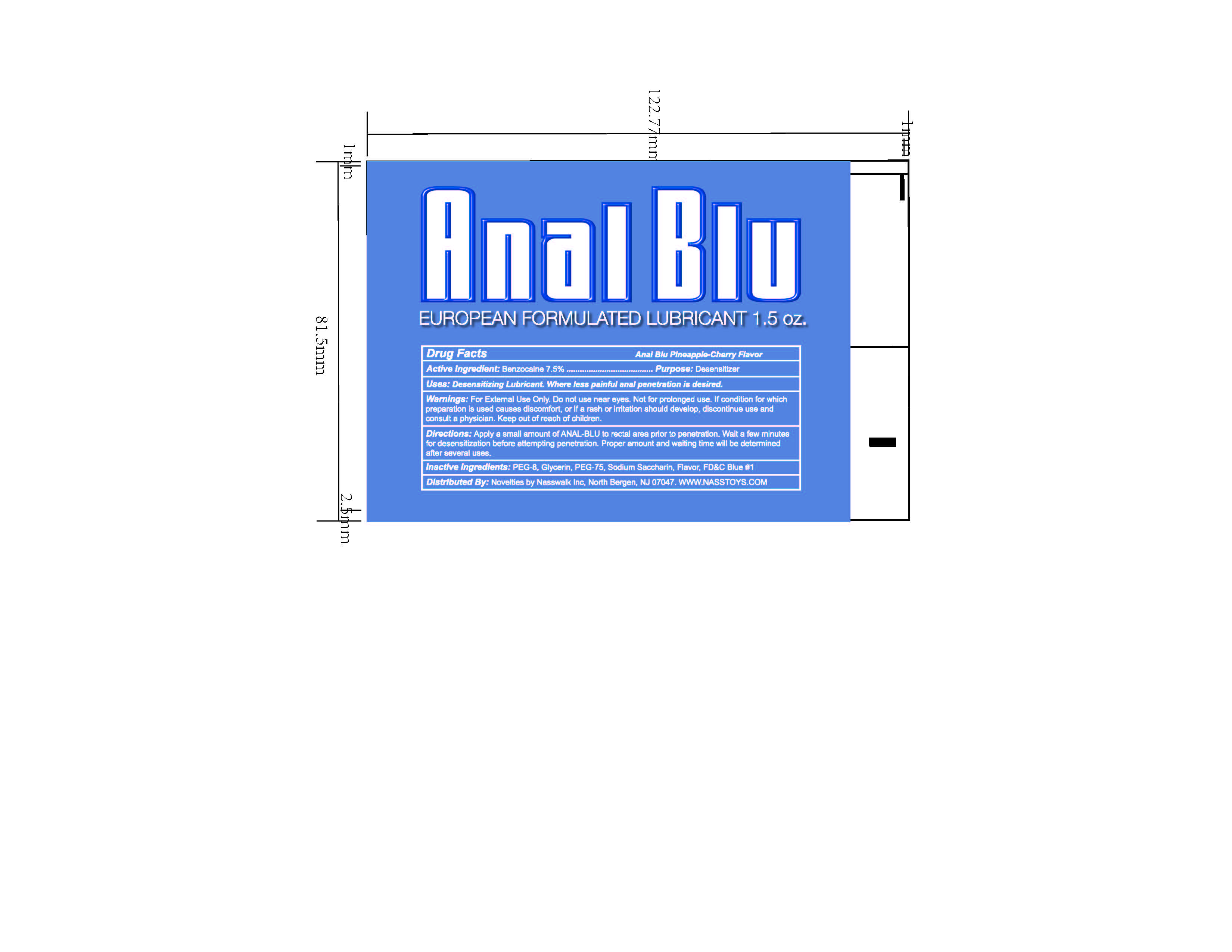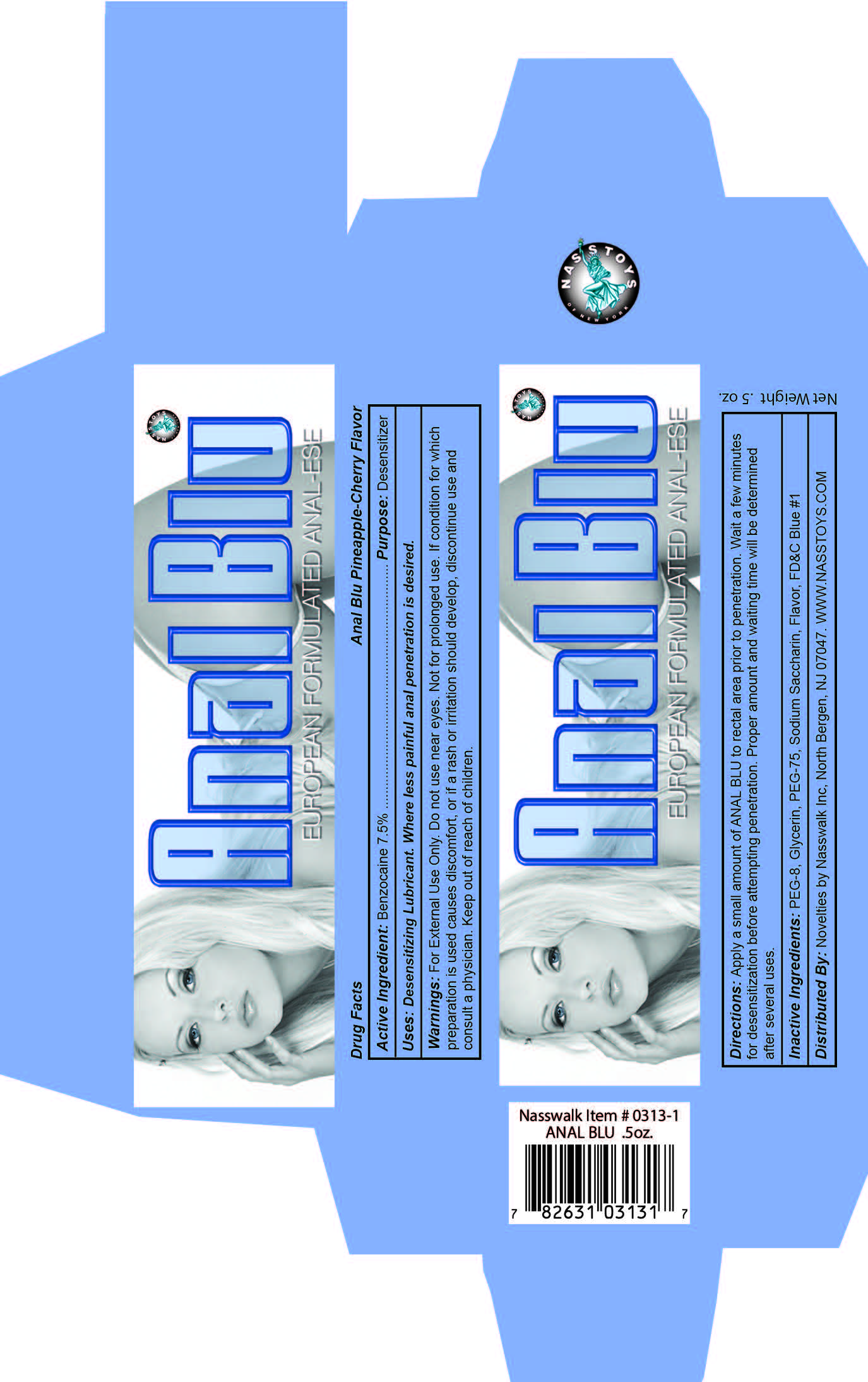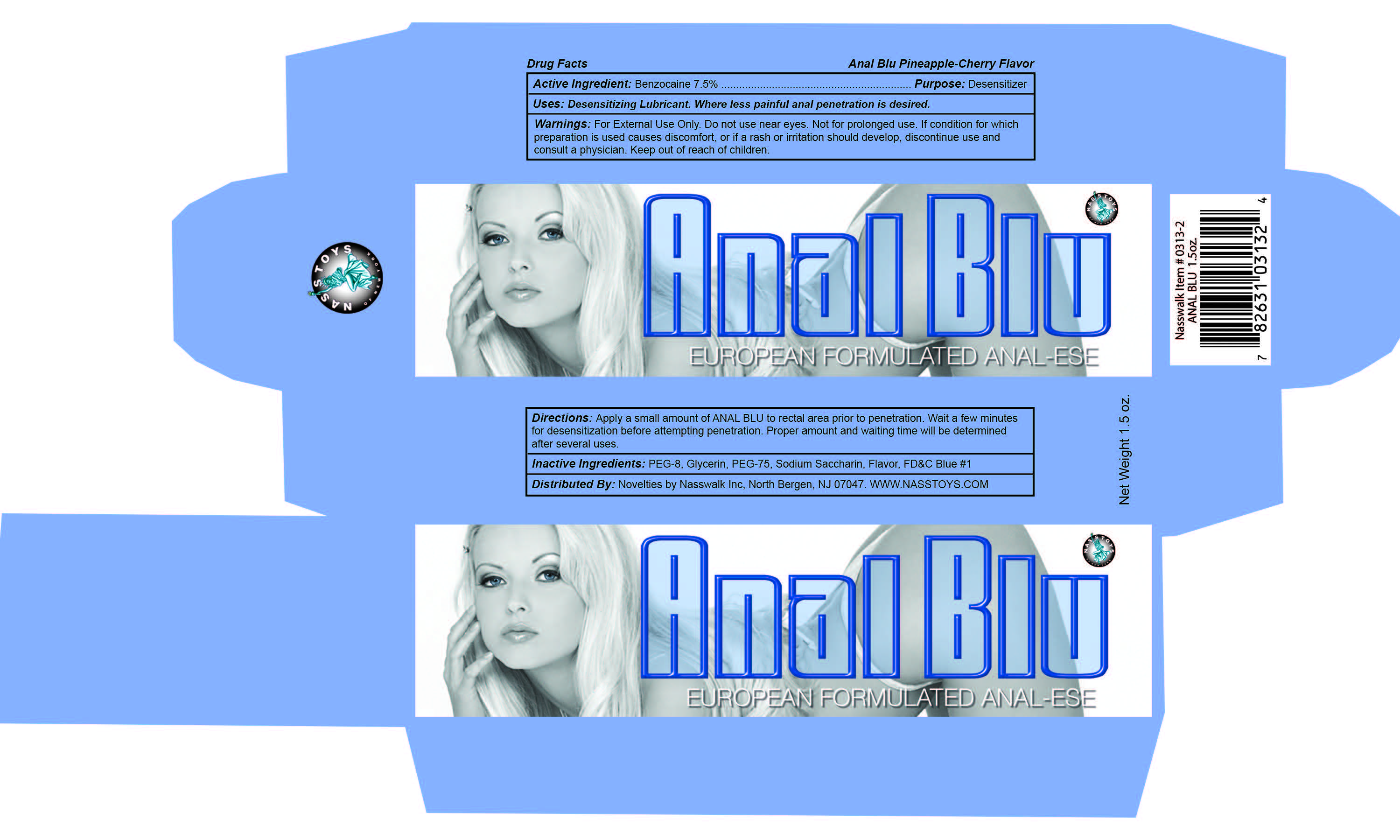 DRUG LABEL: Anal Blu
NDC: 83608-108 | Form: CREAM
Manufacturer: Novelties by Nasswalk, Inc.
Category: otc | Type: HUMAN OTC DRUG LABEL
Date: 20251110

ACTIVE INGREDIENTS: BENZOCAINE 7.5 g/100 mL
INACTIVE INGREDIENTS: GLYCERIN; PEG-8 STEARATE; SACCHARIN SODIUM; FD&C BLUE NO. 1; PEG-75 STEARATE

Anal Blu

Active Ingredient:

Benzocaine 7.5%

Purpose:

Desensitizer

Uses:

Desensitizing Lubricant. Where less painful anal penetration is desired.

Warnings:

For External use only. Do not use near eyes. Not for prolonged use. If condition for which preparation is used causes discomfort, or if a rash or irritation should develop, discontinue use and consult a physician. For prevention of premature ejaculation.

Directions:

Apply a small amount of ANAL BLU to rectal area prior to penetration. Wait a few minutes for desensitization before attempting penetration. Proper amount and waiting time will be determined after seferal uses.

Inactive Ingredients:

PEG-8, Glycerin, PEG-75, Sodium Saccharin, Flavor, FD&C Blue #1

Anal Blu

EUROPEAN FORMULATED ANAL-ESE

Anal Blu Pineapple-Cherry Flavor

Net Weight 1.5 oz.

Distributed By: Novelties by Nasswalk Inc, North Bergeb, NJ 07047. WWW.NASSTOYS.COM

1.5 Carton

1.5 Tube

Net Weight 0.5 oz.

Distributed By: Novelties by Nasswalk Inc, North Bergeb, NJ 07047. WWW.NASSTOYS.COM

0.5 Carton

0.5 Tube